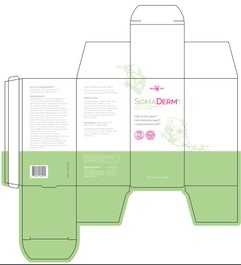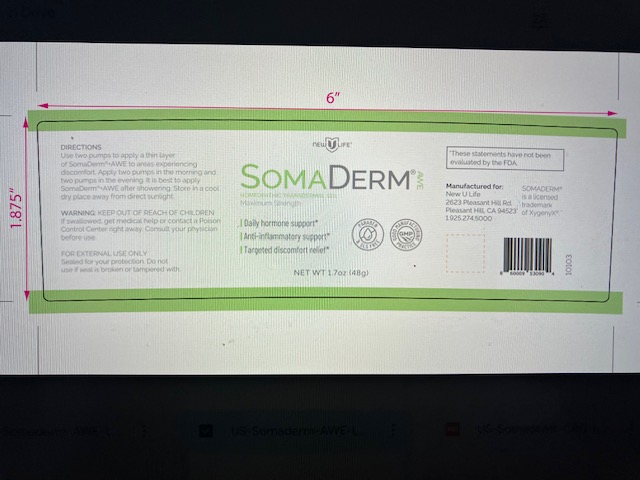 DRUG LABEL: Somaderm AWE
NDC: 61877-0008 | Form: GEL
Manufacturer: Natural Life Foods Corporation dba XYGENYX
Category: homeopathic | Type: HUMAN OTC DRUG LABEL
Date: 20231227

ACTIVE INGREDIENTS: SOMATROPIN 30 [hp_X]/1 g; THYROID, BOVINE 8 [hp_X]/1 g; SUS SCROFA ADRENAL GLAND 6 [hp_X]/1 g
INACTIVE INGREDIENTS: WATER; ARNICA MONTANA FLOWER; ALOE VERA LEAF; LICORICE; VITEX AGNUS-CASTUS LEAF; GINKGO BILOBA WHOLE; DIOSCOREA VILLOSA ROOT; CAPRYLYL GLYCOL; ASCORBIC ACID; PEG-14 DIMETHICONE; ALOE; TOCOPHEROL; POTASSIUM SORBATE; EUCALYPTUS OIL; POLYETHYLENE GLYCOL 100000; WILLOW BARK; PHENOXYETHANOL; SORBIC ACID; COPAIBA OIL; GREEN TEA LEAF; EPIMEDIUM SAGITTATUM LEAF; EDETATE DISODIUM; MENTHA PIPERITA; POLYSORBATE 80; MUCUNA PRURIENS SEED; SODIUM HYDROXIDE; ETHYLENE OXIDE

INACTIVE INGREDIENT

WATER (UNII: 059QF0KO0R)
PHENOXYETHANOL (UNII: HIE492ZZ3T)
CAPRYLYL GLYCOL (UNII: 00YIU5438U)
SORBIC ACID (UNII: X045WJ989B)
ALOE VERA LEAF (UNII: ZY81Z83H0X)
GREEN TEA LEAF (UNII: W2ZU1RY8B0)
CARBOMER INTERPOLYMER TYPE A (ALLYL SUCROSE CROSSLINKED) (UNII: 59TL3WG5CO)
LICORICE (UNII: 61ZBX54883)
CHASTE TREE (UNII: 433OSF3U8A)
EPIMEDIUM SAGITTATUM TOP (UNII: 7G8Y7M4D58)
GINKGO (UNII: 19FUJ2C58T)
MUCUNA PRURIENS SEED (UNII: 55G8SQ543S)
DIOSCOREA VILLOSA TUBER (UNII: IWY3IWX2G8)
SODIUM HYDROXIDE (UNII: 55X04QC32I)
ASCORBIC ACID (UNII: PQ6CK8PD0R)
POLYETHYLENE GLYCOL 1500 (UNII: 1212Z7S33A)
PEG-8 DIMETHICONE (UNII: GIA7T764OD)
POLYETHYLENE GLYCOL 700 (UNII: 762678AC5R)
TOCOPHEROL (UNII: R0ZB2556P8)
EDETATE DISODIUM (UNII: 7FLD91C86K)
OREGANO (UNII: 0E5AT8T16U)
POTASSIUM SORBATE (UNII: 1VPU26JZZ4)

INDICATIONS AND USAGE

MAY IMPROVE BONE AND JOINT HEALTH*MAY INCREASE MUSCLE AND REDUCE FAT*MAY IMPROVE SLEEP*MAY STRENGTHEN THE IMMUNE SYSTEM**These statements have not been evaluated by the FDA MAY IMPROVE BONE AND JOINT HEALTH*MAY INCREASE MUSCLE AND REDUCE FAT*MAY IMPROVE SLEEP*MAY STRENGTHEN THE IMMUNE SYSTEM**These statements have not been evaluated by the FDA

WARNING: KEEP OUT OF REACH OF CHILDREN

If swallowed, get medical help or contact a Poison Control Center right away.

If pregnant or breast-feeding, ask a health professional before use.

FOR EXTERNAL USE ONLY

Sealed for your protection.

Do not use if seal has been broken or tampered with.

INSTRUCTIONS FOR USE

Apply 1 full pump in the morning and 1 full pump in the evening: 5 days on, 2 days off. For intensive use, apply 2 full pumps in the morning, 2 full pumps in the evening.

Gel should always be applied to the thin areas of skin, wherever veins are visible. You may apply the gel to your underarms, forearms, wrists and behind the knees. Applied locations should be rotated.

QUESTIONS:

Distributed By:
XYGENYX
2638 Pleasant Hill Rd,
Pleasant Hill, CA 94523
1-844-510-6398

ACTIVE INGREDIENT

Glandula Suprarenalis Suis 6X, Thyroidinum (Bovine) 8X, Somatropin 30X.

DOSAGE AND ADMINISTRATION

Use two pumps to apply a thin layer of Samderm AQW to areas experiencing discomfort. Apply two pumps in the morning and two pumps in the evening. It is best to apply Somaderm AWE after showering. Store in a cool dry place from direct sunlight.

STORAGE AND HANDLING

Store in a cool dry place away from direct sunlight.

PURPOSE

May Improve Bone and Joint Health*May Increase Muscle and Reduce Fat*May Improve Sleep**These statements have not been evaluated by the FDA May Improve Bone and Joint Health*May Increase Muscle and Reduce Fat*May Improve Sleep**These statements have not been evaluated by the FDA